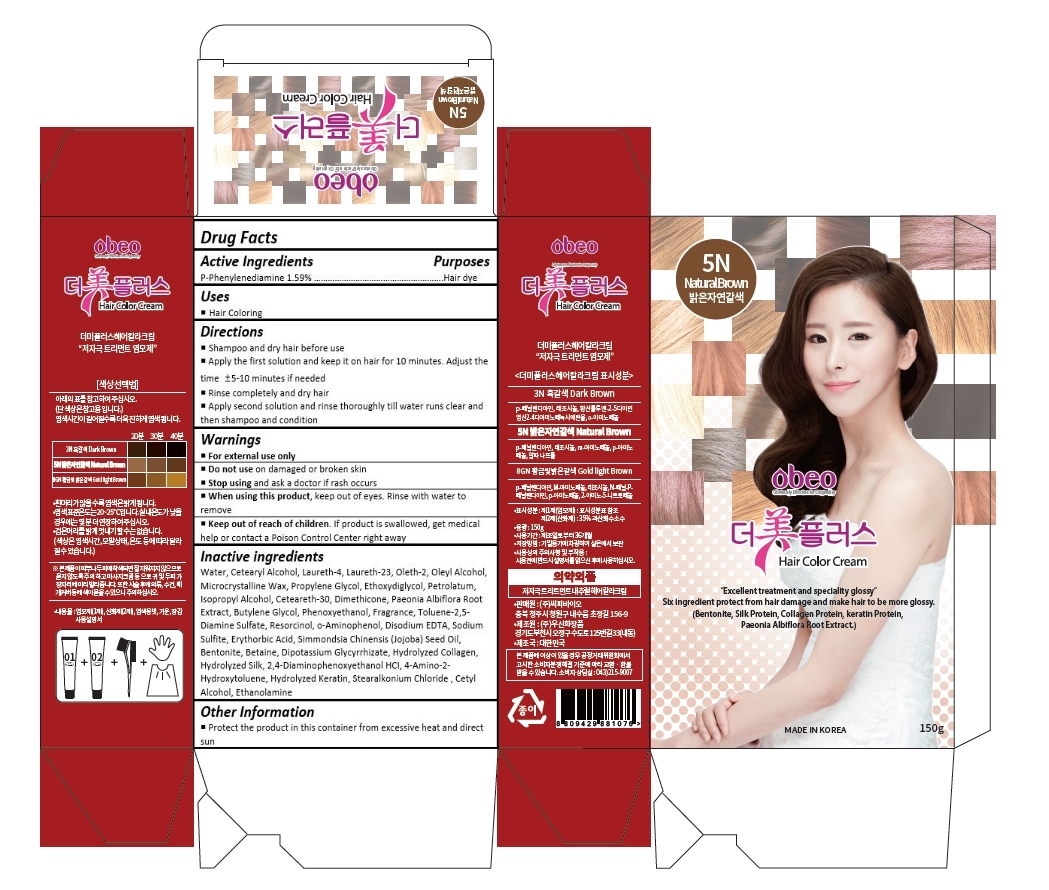 DRUG LABEL: Obeo The Mee Plus Hair Color Cream Natural Brown
NDC: 69871-006 | Form: CREAM
Manufacturer: CPbio Co., Ltd
Category: otc | Type: HUMAN OTC DRUG LABEL
Date: 20160303

ACTIVE INGREDIENTS: P-PHENYLENEDIAMINE 1.2 mg/150 g
INACTIVE INGREDIENTS: WATER; CETOSTEARYL ALCOHOL; LAURETH-4; LAURETH-23; OLETH-2; OLEYL ALCOHOL; MICROCRYSTALLINE WAX; PROPYLENE GLYCOL; DIETHYLENE GLYCOL MONOETHYL ETHER; PETROLATUM; ISOPROPYL ALCOHOL; CETEARETH-30; DIMETHICONE; PAEONIA LACTIFLORA ROOT; BUTYLENE GLYCOL; PHENOXYETHANOL; EDETATE DISODIUM; SODIUM SULFITE; ERYTHORBIC ACID; JOJOBA OIL; RESORCINOL; BENTONITE; BETAINE; GLYCYRRHIZINATE DIPOTASSIUM; M-AMINOPHENOL; 1-NAPHTHOL; P-AMINOPHENOL; STEARALKONIUM CHLORIDE; CETYL ALCOHOL; MONOETHANOLAMINE

Drug Facts

ACTIVE INGREDIENT

P-Phenylenediamine 0.80%

PURPOSE

Hair dye

INDICATIONS AND USAGE

Hair Coloring

DOSAGE AND ADMINISTRATION

Shampoo and dry hair before use
Apply the first solution and keep it on hair for 10 minutes. Adjust the time ±5-10 minutes if needed
Rinse completely and dry hair
Apply second solution and rinse thoroughly till water runs clear and then shampoo and condition

WARNINGS

For external use only

Do not use on damaged or broken skin

Stop using and ask a doctor if rash occurs

When using this product, keep out of eyes. Rinse with water to remove

Keep out of reach of children. If product is swallowed, get medical help or contact a Poison Control Center right away.

INACTIVE INGREDIENT

Water, Cetearyl Alcohol, Laureth-4, Laureth-23, Oleth-2, Oleyl Alcohol, Microcrystalline Wax, Propylene Glycol, Ethoxydiglycol, Petrolatum, Isopropyl Alcohol, Ceteareth-30, Dimethicone, Paeonia Albiflora Root Extract, Butylene Glycol, Phenoxyethanol, Fragrance, Disodium EDTA, Sodium Sulfite, Erythorbic Acid, Simmondsia Chinensis (Jojoba) Seed Oil, Resorcinol, Bentonite, Betaine, Dipotassium Glycyrrhizate, Hydrolyzed Collagen, Hydrolyzed Silk, m-Aminophenol, 1-Naphthol, p-Aminophenol, Hydrolyzed Keratin, Stearalkonium Chloride , Cetyl Alcohol, Ethanolamine